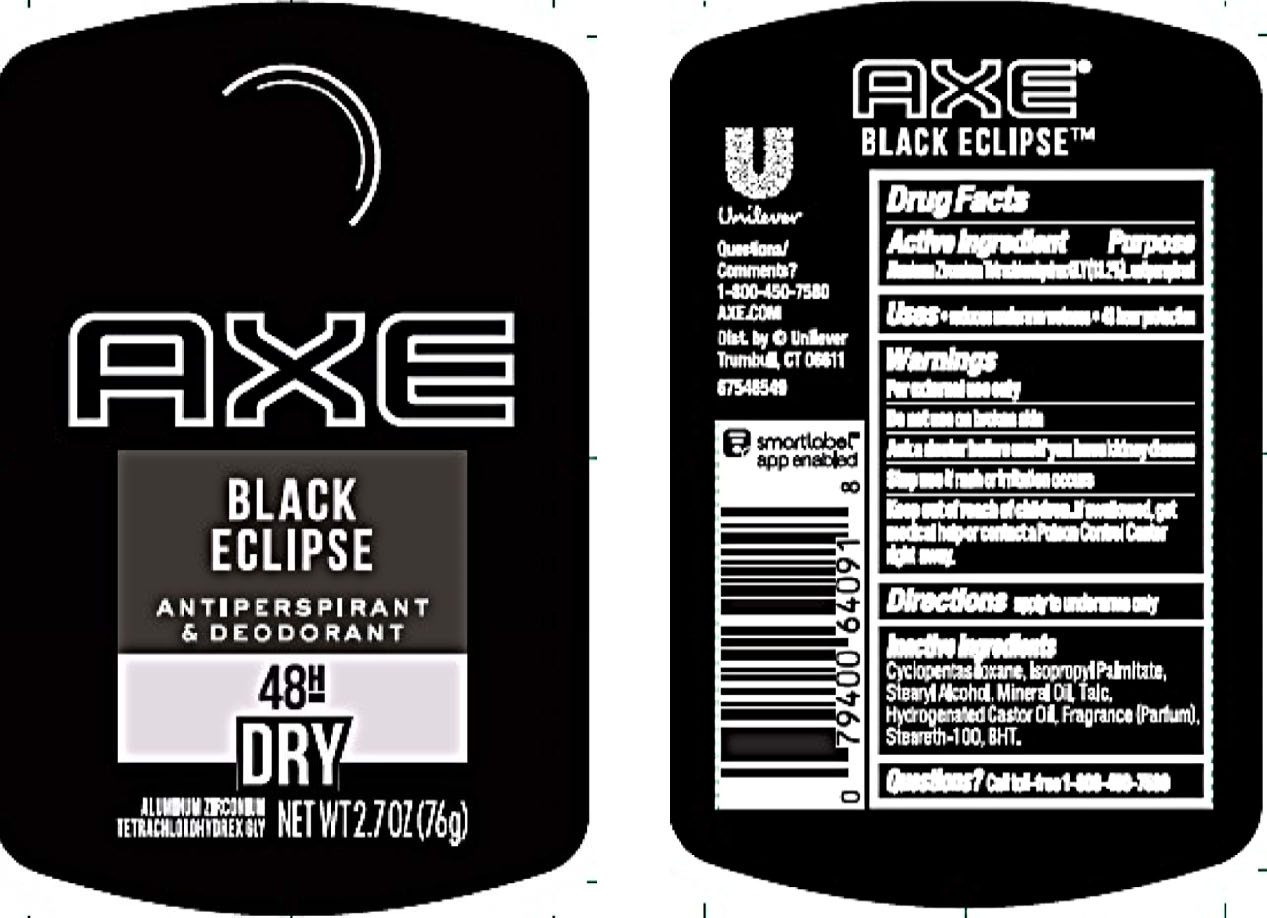 DRUG LABEL: Axe
NDC: 64942-1591 | Form: STICK
Manufacturer: Conopco Inc. d/b/a/ Unilever
Category: otc | Type: HUMAN OTC DRUG LABEL
Date: 20201108

ACTIVE INGREDIENTS: ALUMINUM ZIRCONIUM TETRACHLOROHYDREX GLY 18.2 g/100 g
INACTIVE INGREDIENTS: TALC; CYCLOMETHICONE 5; HYDROGENATED CASTOR OIL; BUTYLATED HYDROXYTOLUENE; STEARYL ALCOHOL; ISOPROPYL PALMITATE; MINERAL OIL; STEARETH-100

Axe Black Eclipse 48H Dry Antiperspirant and Deodorant

AXE BLACK ECLIPSE 48H DRY ANTIPERSPIRANT AND DEODORANT - aluminum zirconium tetrachlorohydrex gly stick

Axe Black Eclipse 48H Dry Antiperspirant and Deodorant

Drug Facts

Active ingredient

Aluminum Zirconium Tetrachlorohydrex GLY (18.2 %)

Purpose

antiperspirant

Uses

• reduces underarm wetness

• 48 Hour Protection

Warnings

• For external use only.
• Do not use on broken skin .
• Ask a doctor before use if you have kidney disease.
• Stop use if rash or irritation occurs.

• Keep out of reach of children.

If swallowed, get medical help or contact a Poison Control Center right away.

Directions

apply to underarms only

Inactive ingredients

Cyclopentasiloxane, Isopropyl Palmitate, Stearyl Alcohol, Mineral Oil, Talc, Hydrogenated Castor Oil, Fragrance (Parfum), Steareth-100, BHT.

Questions?

Call toll-free 1-800-450-7580